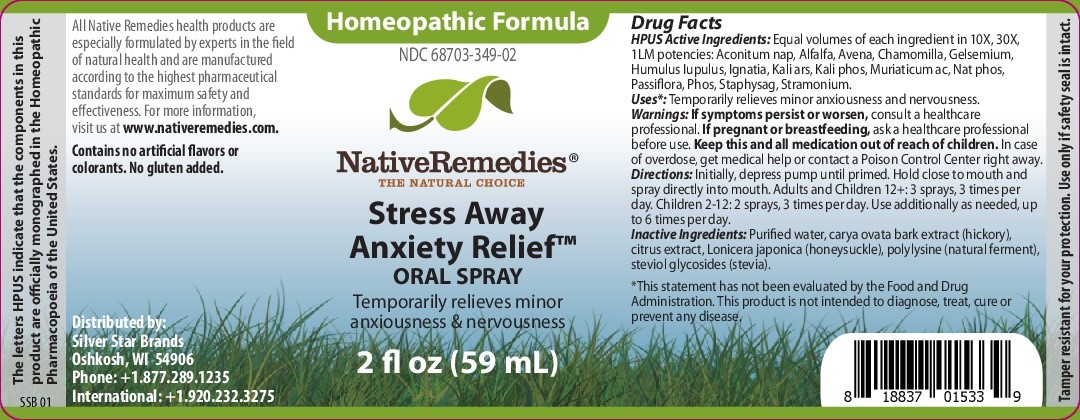 DRUG LABEL: Stress Away Anxiety Relief
NDC: 68703-349 | Form: SPRAY
Manufacturer: Silver Star Brands
Category: homeopathic | Type: HUMAN OTC DRUG LABEL
Date: 20241203

ACTIVE INGREDIENTS: HYDROCHLORIC ACID 10 [hp_X]/59 mL; PHOSPHORUS P-32 10 [hp_X]/59 mL; DATURA STRAMONIUM 10 [hp_X]/59 mL; DELPHINIUM STAPHISAGRIA SEED 10 [hp_X]/59 mL; ALFALFA 10 [hp_X]/59 mL; MATRICARIA CHAMOMILLA FLOWERING TOP OIL 10 [hp_X]/59 mL; POTASSIUM PHOSPHATE, UNSPECIFIED FORM 10 [hp_X]/59 mL; SODIUM PHOSPHATE, DIBASIC 10 [hp_X]/59 mL; ACONITUM NAPELLUS 10 [hp_X]/59 mL; GELSEMIUM SEMPERVIRENS ROOT 10 [hp_X]/59 mL; HUMULUS LUPULUS WHOLE 10 [hp_X]/59 mL; STRYCHNOS IGNATII WHOLE 10 [hp_X]/59 mL; POTASSIUM ARSENITE ANHYDROUS 10 [hp_X]/59 mL; PASSIFLORA INCARNATA FLOWERING TOP 10 [hp_X]/59 mL; AVENA SATIVA LEAF 10 [hp_X]/59 mL
INACTIVE INGREDIENTS: ANHYDROUS CITRIC ACID; POLY-L-LYSINE (30000-70000 MW); WATER; CARYA OVATA BARK; LONICERA JAPONICA FLOWER; GLUCOSYL STEVIOL

NativeRemedies® Stress Away Anxiety Relief Oral Spray

Active Ingredients

HPUS Active Ingredients: Equal volumes of each ingredient in 10X, 30X, 1LM potencies: Aconitum nap, Alfalfa, Avena, Chamomilla, Gelsemium, Humulus lupulus, Ignatia, Kali ars, Kali phos, Muriaticum ac, Nat phos, Passiflora, Phos, Staphysag, Stamonium.

Uses*

Uses*: Temporarily relieves minor anxiousness and nervousness.

Warnings

Warnings: If symptoms persist or worsen, consult a healthcare professional. If pregnant or breastfeeding, ask a healthcare professional before use. Keep this and all medication away from children. In case of overdose, get medical help or contact a Poison Control Center right away.

Directions

Directions: Initially, depress pump until primed. Hold close to mouth and spray directly into mouth. Adults and Children 12+: 3 sprays, 3 times per day. children 1-12: 2 sprays, 3 time per day. Use additionally as needed, up to 6 times per day.

OTHER SAFETY INFORMATION

Contains no artificial flavors or colorants. No gluten added.

Tamper resistant for your protection. use only if saftey seal is intact.

Inactive Ingredients

Inactive Ingredients: Purified water, carya ovata bark extract (hickory), citrust extract, Lonicera japonica (honeysuckle), plylysine (natural ferment), steviol glycosides (stevia).

KEEP OUT OF REACH OF CHILDREN

keep this and all medication out of reach of children.

PREGNANCY OR BREAST FEEDING

If pregnant or breastfeeding, ask a healthcare professional before use.

PURPOSE

Temporarily relieves minor anxiousness & nervousness.